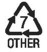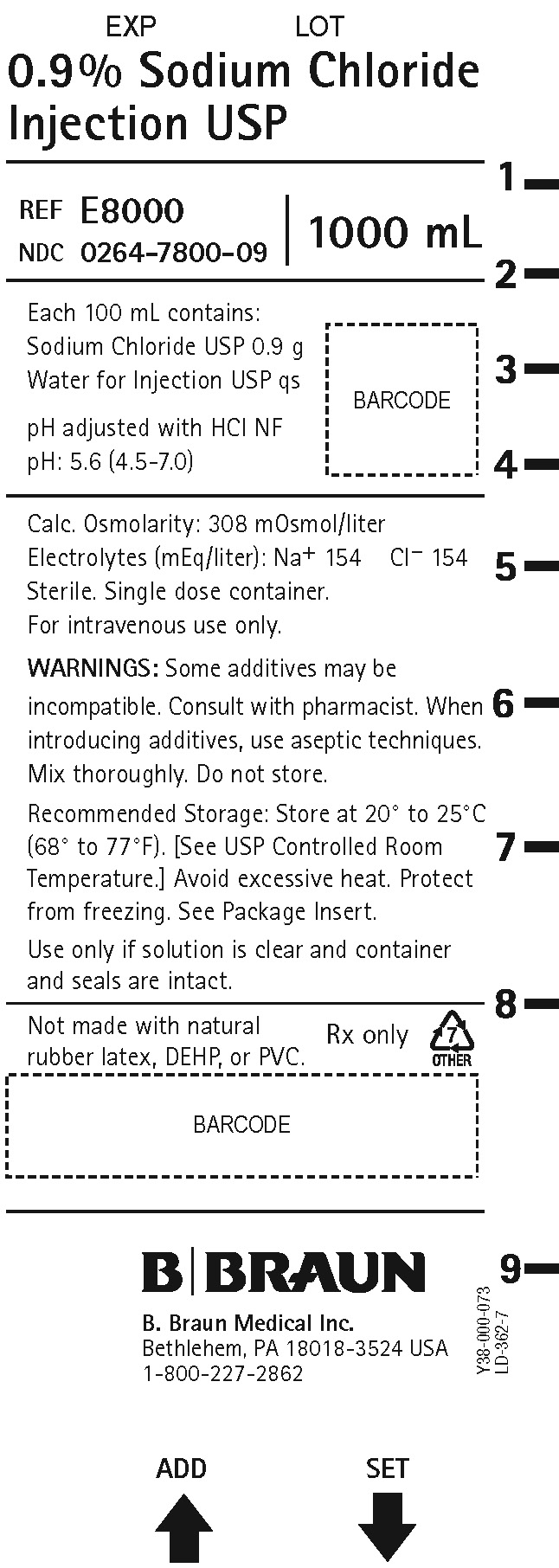 DRUG LABEL: Sodium Chloride
NDC: 0264-7800 | Form: INJECTION, SOLUTION
Manufacturer: B. Braun Medical Inc.
Category: prescription | Type: HUMAN PRESCRIPTION DRUG LABEL
Date: 20240508

ACTIVE INGREDIENTS: SODIUM CHLORIDE 0.9 g/100 mL
INACTIVE INGREDIENTS: WATER

0.9% Sodium Chloride Injection USP

DESCRIPTION

Each 100 mL of 0.9% Sodium Chloride Injection USP contains:

Sodium Chloride USP 0.9 g; Water for Injection USP qs

pH: 5.6 (4.5-7.0)

Calculated Osmolarity: 308 mOsmol/liter

pH adjusted with Hydrochloric Acid NF

Concentration of Electrolytes (mEq/liter): Sodium 154; Chloride 154

Sodium Chloride Injection USP is sterile, nonpyrogenic, isotonic and contains no bacteriostatic or antimicrobial agents.

The formula of the active ingredient is:

Ingredient | Molecular Formula | Molecular Weight
Sodium Chloride USP | NaCl | 58.44

Not made with natural rubber latex, PVC, or DEHP.

The plastic container is made from a homogenous blend of polypropylene and thermoplastic modifier specifically developed for parenteral drugs. The container is nontoxic and biologically inert. The container is a closed system and is not dependent upon entry of external air during administration.

Addition of medication should be accomplished using complete aseptic technique.

The closure system has two ports; one for the administration set and the other is a medication addition site. Each port has a tamper evident cover. Refer to the Directions for Use of the container.

CLINICAL PHARMACOLOGY

Sodium Chloride Injection USP provides electrolytes and is a source of water for hydration. It is capable of inducing diuresis depending on the clinical condition of the patient.

Sodium, the major cation of the extracellular fluid, functions primarily in the control of water distribution, fluid balance, and osmotic pressure of body fluids. Sodium is also associated with chloride and bicarbonate in the regulation of the acid-base equilibrium of body fluid.

Chloride, the major extracellular anion, closely follows the metabolism of sodium, and changes in the acid-base balance of the body are reflected by changes in the chloride concentration.

INDICATIONS AND USAGE

This intravenous solution is indicated for use in adults and pediatric patients as a source of electrolytes and water for hydration.

0.9% Sodium Chloride Injection USP is indicated for extracellular fluid replacement, treatment of metabolic alkalosis in the presence of fluid loss and mild sodium depletion.

0.9% Sodium Chloride Injection USP is also indicated for use as a priming solution in hemodialysis procedures and may be used to initiate and terminate blood transfusions without hemolyzing red blood cells.

Sodium Chloride Injection USP is also indicated as a pharmaceutic aid and diluent for the infusion of compatible drug additives. Refer to prescribing information accompanying additive drugs.

CONTRAINDICATIONS

This solution is contraindicated where the administration of sodium or chloride could be clinically detrimental.

WARNINGS

The administration of intravenous solutions can cause fluid and/or solute overload resulting in dilution of serum electrolyte concentrations, overhydration, congested states or pulmonary edema. The risk of dilutional states is inversely proportional to the electrolyte concentration. The risk of solute overload causing congested states with peripheral and pulmonary edema is directly proportional to the electrolyte concentration.

Solutions containing sodium ions should be used with great care, if at all, in patients with congestive heart failure, severe renal insufficiency, and in clinical states in which there is sodium retention with edema. In patients with diminished renal function, administration of solutions containing sodium ions may result in sodium retention.

Infusion of isotonic (0.9%) sodium chloride during or immediately after surgery may result in excessive sodium retention. Use the patient’s circulatory system status as a guide.

PRECAUTIONS

General

Clinical evaluation and periodic laboratory determinations are necessary to monitor changes in fluid balance, electrolyte concentrations, and acid-base balance during prolonged parenteral therapy or whenever the condition of the patient warrants such evaluation. Significant deviations from normal concentrations may require tailoring of the electrolyte pattern, in these or alternative solutions.

This solution should be used with care in patients with hypervolemia, renal insufficiency, urinary tract obstruction, or impending or frank cardiac decompensation.

Extraordinary electrolyte losses such as may occur during protracted nasogastric suction, vomiting, diarrhea or gastrointestinal fistula drainage may necessitate additional electrolyte supplementation. Additional essential electrolytes, minerals and vitamins should be supplied as needed.

Sodium-containing solutions should be administered with caution to patients receiving corticosteroids or corticotropin, or to other salt-retaining patients. Care should be exercised in administering solutions containing sodium to patients with renal or cardiovascular insufficiency, with or without congestive heart failure, particularly if they are postoperative or elderly.

Infusion of more than one liter of isotonic (0.9%) sodium chloride per day may supply more sodium and chloride than normally found in serum, and can exceed normal tolerance, resulting in hypernatremia; this may also cause a loss of bicarbonate ions, resulting in an acidifying effect.

To minimize the risk of possible incompatibilities arising from mixing this solution with other additives that may be prescribed, the final infusate should be inspected for cloudiness or precipitation immediately after mixing, prior to administration and periodically during administration.

Do not use plastic container in series connection.

If administration is controlled by a pumping device, care must be taken to discontinue pumping action before the container runs dry or air embolism may result.

This solution is intended for intravenous administration using sterile equipment. It is recommended that intravenous administration apparatus be replaced at least once every 24 hours.

Use only if solution is clear and container and seals are intact.

Carcinogenesis, Mutagenesis, Impairment of Fertility

Studies with Sodium Chloride Injection USP have not been performed to evaluate carcinogenic potential, mutagenic potential or effects on fertility.

Pregnancy

- Teratogenic Effects

Animal reproduction studies have not been conducted with Sodium Chloride Injection USP. It is also not known whether Sodium Chloride Injection USP can cause fetal harm when administered to a pregnant woman or can affect reproduction capacity. Sodium Chloride Injection USP should be given to a pregnant woman only if clearly needed.

Nursing Mothers

It is not known whether this drug is excreted in human milk. Because many drugs are excreted in human milk, caution should be exercised when Sodium Chloride Injection USP is administered to a nursing woman.

Pediatric Use

Safety and effectiveness of sodium chloride injections in pediatric patients have not been established by adequate and well controlled trials, however, the use of electrolyte solutions in the pediatric population is referenced in the medical literature. The warnings, precautions and adverse reactions identified in the label copy should be observed in the pediatric population.

Geriatric Use

An evaluation of current literature revealed no clinical experience identifying differences in response between elderly and younger patients. In general, dose selection for an elderly patient should be cautious, usually starting at the low end of the dosing range, reflecting the greater frequency of decreased hepatic, renal, or cardiac function, and of concomitant disease or other drug therapy.

This drug is known to be substantially excreted by the kidney, and the risk of toxic reactions may be greater in patients with impaired renal function. Because elderly patients are more likely to have decreased renal function, care should be taken in dose selection, and it may be useful to monitor renal function.

ADVERSE REACTIONS

Reactions which may occur because of the solution or the technique of administration include febrile response, infection at the site of injection, venous thrombosis or phlebitis extending from the site of injection, extravasation and hypervolemia.

The physician should also be alert to the possibility of adverse reactions to drug additives. Prescribing information for drug additives to be administered in this manner should be consulted.

Symptoms may result from an excess or deficit of one or more of the ions present in the solution; therefore, frequent monitoring of electrolyte levels is essential.

Hypernatremia may be associated with edema and exacerbation of congestive heart failure due to the retention of water, resulting in an expanded extracellular fluid volume.

If infused in large amounts, chloride ions may cause a loss of bicarbonate ions, resulting in an acidifying effect.

If an adverse reaction does occur, discontinue the infusion, evaluate the patient, institute appropriate therapeutic countermeasures, and save the remainder of the fluid for examination if deemed necessary.

OVERDOSAGE

In the event of a fluid or solute overload during parenteral therapy, reevaluate the patient’s condition and institute appropriate corrective treatment.

DOSAGE AND ADMINISTRATION

This solution is for intravenous use only.

Dosage is to be directed by a physician and is dependent upon age, weight, clinical condition of the patient and laboratory determinations. Frequent laboratory determinations and clinical evaluation are essential to monitor changes in blood glucose and electrolyte concentrations, and fluid and electrolyte balance during prolonged parenteral therapy.

In the average adult, daily requirements of sodium and chloride are met by the infusion of one liter of 0.9% sodium chloride (154 mEq each of sodium and chloride).

There is no specific pediatric dose. The dose is dependent on weight, clinical condition and laboratory results. Follow recommendations of appropriate pediatric reference text. (See PRECAUTIONS, Pediatric Use.)

Fluid administration should be based on calculated maintenance or replacement fluid requirements for each patient.

0.9% Sodium Chloride Injection USP may also be administered intravascularly as a priming fluid in hemodialysis procedures.

When Sodium Chloride Injection USP is used as a diluent for infusion of compatible drug additives, refer to dosage and administration information accompanying additive drugs.

Some additives may be incompatible. Consult with pharmacist. When introducing additives, use aseptic techniques. Mix thoroughly. Do not store.

Parenteral drug products should be inspected visually for particulate matter and discoloration prior to administration, whenever solution and container permit.

HOW SUPPLIED

Sodium Chloride Injection USP is supplied sterile and nonpyrogenic in Plastic Containers packaged 12 per case.

NDC | REF | Size
0264-7800-09 | E8000 | 1000 mL

Exposure of pharmaceutical products to heat should be minimized. Avoid excessive heat. Protect from freezing. Store at 20° to 25°C (68° to 77°F); excursions permitted between 15° to 30°C (59° to 86°F). [See USP Controlled Room Temperature.]

Directions for Use of Plastic Container

Caution: Do not use plastic container in series connection.

To Open

Check for minute leaks by squeezing solution container firmly. If leaks are found, discard solution as sterility may be impaired. If supplemental medication is desired, follow directions below before preparing for administration.

NOTE: Before use, perform the following checks:

Inspect each container. Read the label. Ensure solution is the one ordered and is within the expiration date.

Invert container and carefully inspect the solution in good light for cloudiness, haze, or particulate matter. Any container which is suspect should not be used.

Use only if solution is clear and container and seals are intact.

Preparation for Administration

1. Remove plastic protector from sterile set port at bottom of container.
2. Attach administration set. Refer to complete directions accompanying set.

To Add Medication

Warning: Some additives may be incompatible.

To Add Medication Before Solution Administration

1. Prepare medication site by removing the additive port closure. Swab the exposed medication site before puncturing.
2. Using syringe with 18-22 Ga. needle, puncture medication port and inner diaphragm and inject.
3. Squeeze and tap ports while ports are upright and mix solution and medication thoroughly.

To Add Medication During Solution Administration

1. Close clamp on the set.
2. Prepare medication site by removing the additive port closure. Swab the exposed medication site before puncturing.
3. Using syringe with 18-22 Ga. needle of appropriate length (at least 5/8 inch), puncture resealable medication port and inner diaphragm and inject.
4. Remove container from IV pole and/or turn to an upright position.
5. Evacuate both ports by tapping and squeezing them while container is in the upright position.
6. Mix solution and medication thoroughly.
7. Return container to in use position and continue administration.

Revised: December 2022

LD-436-4 Y36-003-070

Package Insert

Rx only

B. Braun Medical Inc.
Bethlehem, PA 18018-3524 USA
1-800-227-2862

PRINCIPAL DISPLAY PANEL

0.9% Sodium Chloride Injection USP

REF E8000
NDC 0264-7800-09

1000 mL

Each 100 mL contains:
Sodium Chloride USP 0.9 g
Water for Injection USP qs

pH adjusted with HCl NF
pH: 5.6 (4.5-7.0)

Calc. Osmolarity: 308 mOsmol/liter
Electrolytes (mEq/liter): Na^+ 154 Cl^– 154
Sterile. Single dose container.
For intravenous use only.

WARNINGS: Some additives may be incompatible. Consult with pharmacist. When introducing additives, use aseptic techniques. Mix thoroughly. Do not store.

Recommended Storage: Store at 20° to 25°C (68° to 77°F). [See USP Controlled Room Temperature.] Avoid excessive heat. Protect from freezing. See Package Insert.

Use only if solution is clear and container and seals are intact.

Not made with natural rubber latex, DEHP, or PVC.

Rx only

B. Braun Medical Inc.
Bethlehem, PA 18018-3524 USA
1-800-227-2862

Y38-000-073 LD-362-7

ADD SET

LOT

EXP

E8000